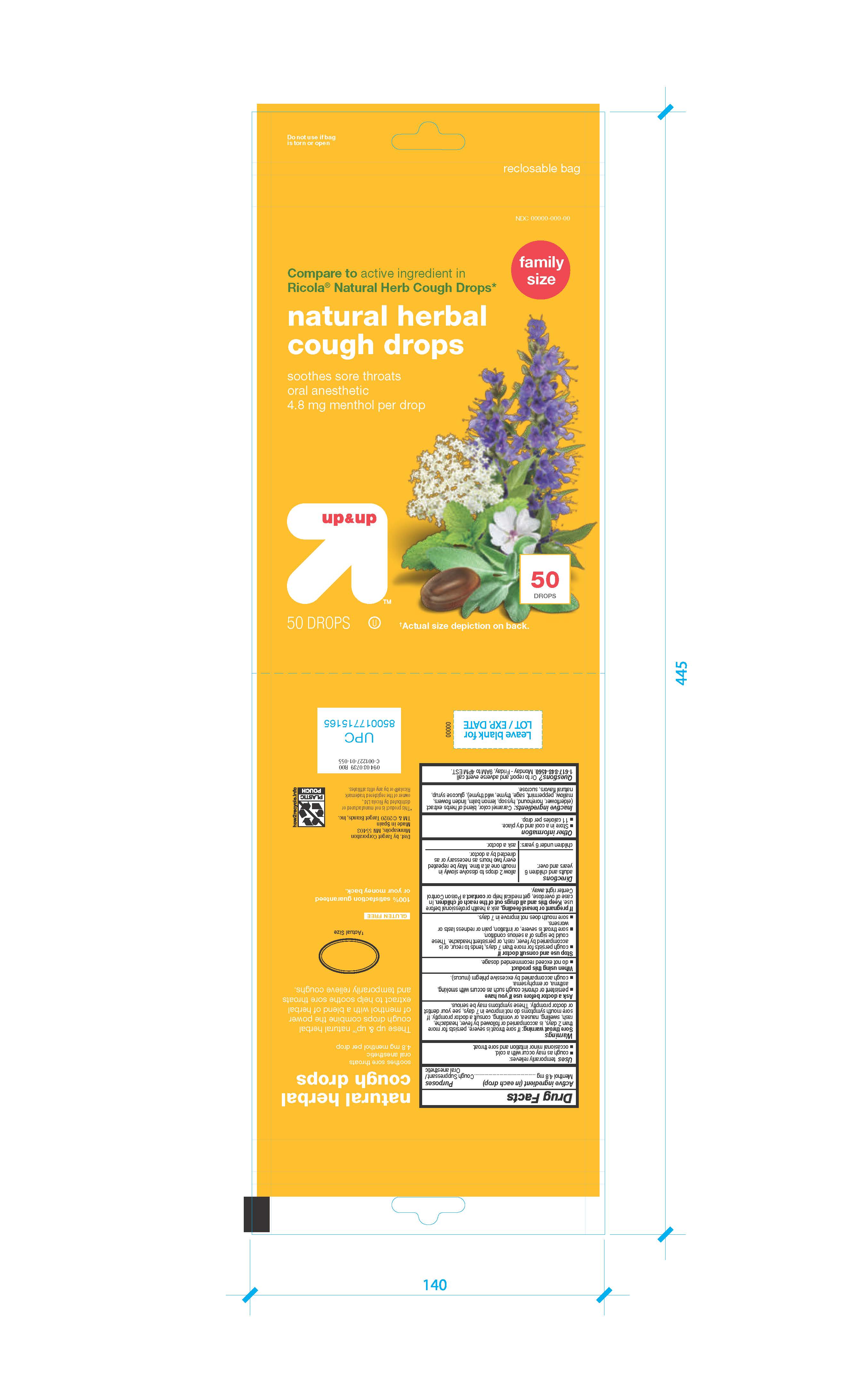 DRUG LABEL: Natural Herbal Cough Drops
NDC: 11673-144 | Form: PASTILLE
Manufacturer: Target Corporation Inc.
Category: otc | Type: HUMAN OTC DRUG LABEL
Date: 20241007

ACTIVE INGREDIENTS: MENTHOL 4.8 mg/1 1
INACTIVE INGREDIENTS: CARAMEL; HOREHOUND; SAMBUCUS NIGRA FLOWER; HYSSOPUS OFFICINALIS FLOWERING TOP; SUCROSE; CORN SYRUP; THYME; LEMON BALM OIL; PEPPERMINT; LEVOISOMETHADONE; WILD THYME; SAGE; MALVA SYLVESTRIS LEAF

Natural Herbal Cough Drops
50 Drops

Active Ingredient in each drop Purposes

Menthol 20mg Cough Suppressant

Oral anesthetic

PURPOSE

Uses Temporarily relieves:

- cough as may occur with a cold
- ocasional minor irritation and sore throat

INDICATIONS AND USAGE

Uses Temporarily relieves:

- cough as may occur with a cold
- ocasional minor irritation and sore throat

Warnings

Sore throat warning: if sore throat is severe, persist for more than 2 days, is accompanied or followed by fever, headache, rash, swelling, nausea and vomiting consult a doctor promptly. If sore mouth symptons do not improve in 7 days see your dentist or doctor promptly. These symptons may be serious.

Ask a doctor before use if you have

- persistent or chronic cough such as occurs with smoking, asthma or emphysema
- cough accompanied by excessive phlegm (mucus)

Stop use and consult a doctor if

- cough persists more than 7 days, tends to recur or is accompanied by fever, headache, rash or persistent headache. These could be signs of serious conditions.
- sore throat is severe or irritation, pain or redness last or worsens
- sore mouth does not improve in 7 days

PREGNANCY OR BREAST FEEDING

If pregnant or breast-feeding, ask a health professional before use.

KEEP OUT OF REACH OF CHILDREN

Keep this and all drugs out of the reach of children.

OVERDOSAGE

In case of accidental overdose, get medical help or contact a Poison Control Center right away.

Directions

- Adults and children 12 years and over: allow 2 drops slowly in mouth one a time. Maybe repeated every 2 hours as necessary or as directed by a doctor.
- Children under 6 years ask a doctor

OTHER SAFETY INFORMATION

- Store in a cool and dry place

INACTIVE INGREDIENT

GLUCOSE SYRUP, SUCROSE, CARAMEL COLOR, ELDERFLOWER, HONEHOUND, HYSSOP, LEMON BALM, LIDEN FIWER, MALOW, PEPPERMINT, SAGE, THYME, WILD THYME, Natural flavours

QUESTIONS

Questions? or to report and adverse event call: 1-617-848-4560

Monday to Friday 9AM to 4 PM east